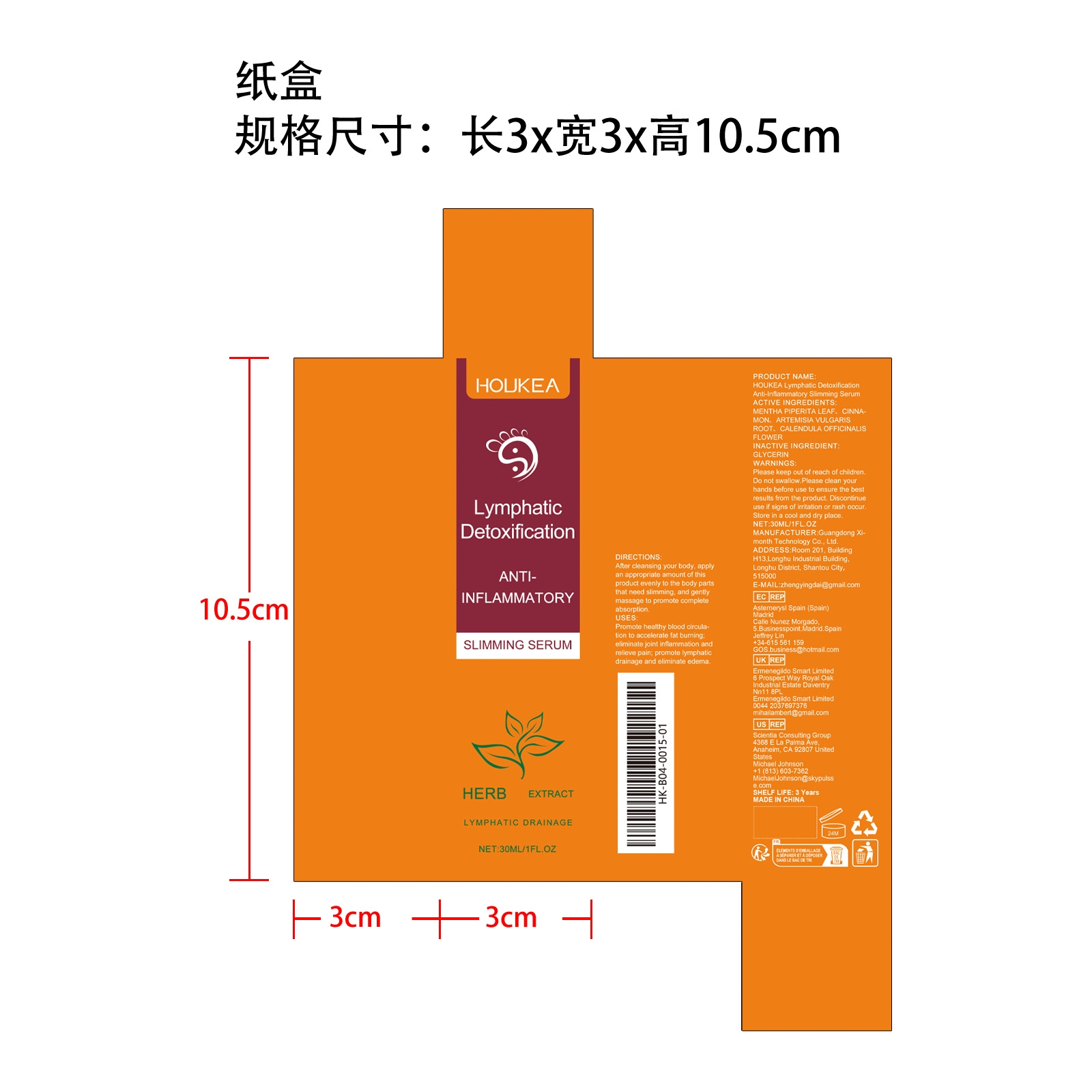 DRUG LABEL: HOUKEA Lymphatic Detoxification Anti-Inflammatory Slimming Serum
NDC: 84660-103 | Form: LIQUID
Manufacturer: Guangdong Ximonth Technology Co., Ltd.
Category: otc | Type: HUMAN OTC DRUG LABEL
Date: 20241101

ACTIVE INGREDIENTS: ARTEMISIA VULGARIS ROOT 4.5 mg/30 mg; CINNAMON 3 mg/30 mg; CALENDULA OFFICINALIS FLOWER 4.5 mg/30 mg; MENTHA PIPERITA LEAF 9 mg/30 mg
INACTIVE INGREDIENTS: GLYCERIN 9 mg/30 mg

ACTIVE INGREDIENTS

MENTHA PIPERITA LEAF,CINNAMON,ARTEMISIA VULGARIS ROOT,CALENDULA OFFICINALIS FLOWER

purpose

Promote healthy blood circulation to accelerate fat burning; eliminate joint inflammation and relieve pain; promote lymphatic drainage and eliminate edema.

uses

After cleansing your body, apply an appropriate amount of this product evenly to the body parts that need slimming, and gently massage to promote complete absorption.

WARNINGS

Please keep out of reach of children. Do not swallow.Please clean your hands before use to ensure the best results from the product. Discontinue use if signs of irritation or rash occur. Store in a cool and dry place.

stop use

Discontinue use if signs of irritation or rash occur.

DO NOT USE

Discontinue use if signs of irritation or rash occur.

KEEP OUT OF REACH OF CHILDREN

Please keep out of reach of children. Do not swallow.

STORAGE AND HANDLING

Store in a cool and dry place.

INACTIVE INGREDIENT

GLYCERIN